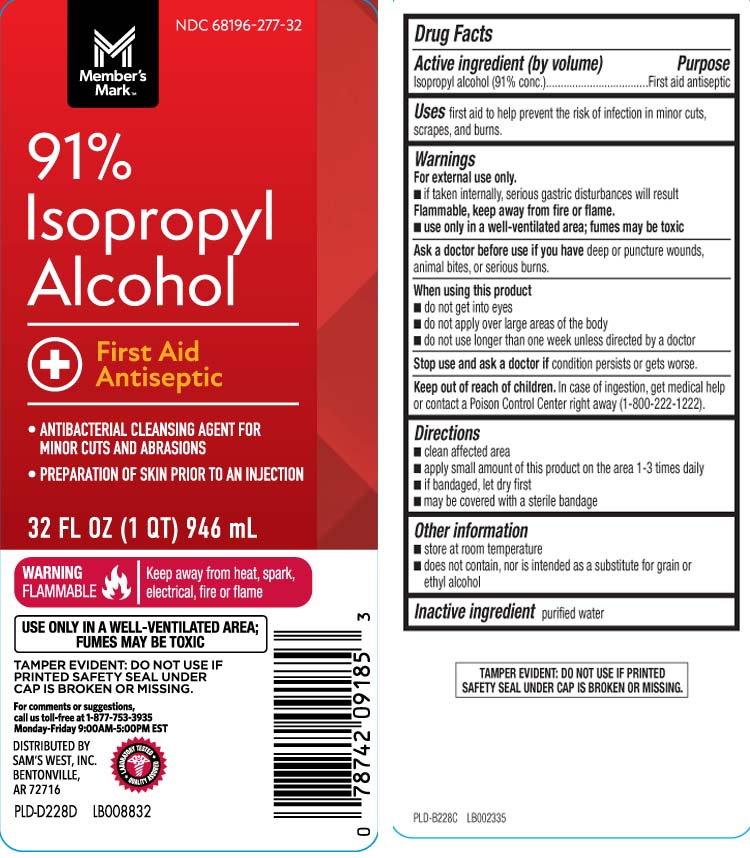 DRUG LABEL: Isopropyl alcohol
NDC: 68196-277 | Form: LIQUID
Manufacturer: Sam's West, Inc
Category: otc | Type: HUMAN OTC DRUG LABEL
Date: 20260302

ACTIVE INGREDIENTS: ISOPROPYL ALCOHOL 91 mL/100 mL
INACTIVE INGREDIENTS: WATER

Drug Facts

Active ingredient (by volume)

Isopropyl alcohol (91% conc.)

Purpose

First aid antiseptic

Uses

- first aid to help prevent the risk of infection in minor cuts, scrapes and burns

Warnings

For external use only.

- if taken internally serious gastric disturbances will result

Flammable, keep away from fire or flame.

- use only in a well-ventilated area; fumes may be toxic

Ask a doctor before use if you have

deep or puncture wounds, animal bites, or serious burns.

When using this product

- do not get into eyes
- do not apply over large areas of the body
- do not use longer than one week unless directed by a doctor

Stop use and ask a doctor if

condition persists or gets worse

Keep out of reach of children.

In case of ingestion, get medical help or contact a Poison Control Center right away (1-800-222-1222).

Directions

- clean affected area
- apply small amount of this product on the area 1-3 times daily
- if bandaged, let dry first
- may be covered with a sterile bandage

Other information

- store at room temperature
- does not contain, nor is intended as a substitute for grain or ethyl alcohol

Inactive ingredient

purified water

Principal Display Panel

91% Isopropyl Alcohol

First Aid Antiseptic

- ANTIBACTERIAL CLEANSING AGENT FOR MINOR CUTS AND ABRASIONS
- PREPARATION OF SKIN PRIOR TO AN INJECTION

WARNING FLAMMABLE keep away from heat, spark, electrical, fire or flame

USE ONLY IN A WELL-VENTILATED AREA; FUMES MAY BE TOXIC

FL OZ (mL)

For comments or suggestions,

call us toll-free at 1-877-753-3935

Monday-Friday 9:00AM-5:00PM EST

TAMPER EVIDENT: DO NOT USE IF PRINTED SAFETY SEAL UNDER CAP IS BROKEN OR MISSING.

DISTRIBUTED BY

SAM'S WEST, INC.

BENTONVILLE,

AR 72716

Package Label

MEMBER'S MARK (Sam's West) 91% Isopropyl Alcohol